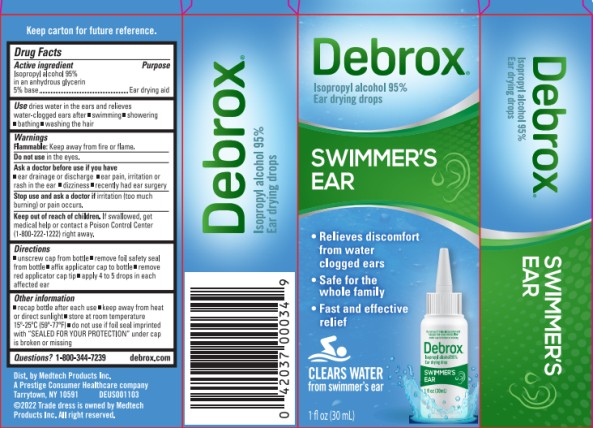 DRUG LABEL: Debrox Swimmers Ear
NDC: 63029-323 | Form: LIQUID
Manufacturer: Medtech Products Inc.
Category: otc | Type: HUMAN OTC DRUG LABEL
Date: 20251023

ACTIVE INGREDIENTS: ISOPROPYL ALCOHOL 95 mL/100 mL
INACTIVE INGREDIENTS: GLYCERIN

Debrox Swimmers Ear

Drug Facts

Active ingredient

Isopropyl alcohol 95% in an anhydrous glycerin 5% base

Purpose

Ear drying aid

Use

dries water in the ears and relieves water-clogged ears after

- swimming
- showering
- bathing
- washing the hair

Warnings

Flammable: Keep away from fire or flame

Do not use

in the eyes

Ask a doctor before use if you have

- ear drainage or discharge
- ear pain, irritation or rash in the ear
- dizziness
- recently had ear surgery

Stop use and ask a doctor if

irritation (too much burning) or pain occurs

Keep out of reach of children.

If swallowed, get medical help or contact a Poison

Control Center (1-800-222-1222) right away.

Directions

- unscrew cap from bottle
- remove foil safety seal from bottle
- affix applicator cap to bottle
- remove red applicator cap tip
- apply 4 to 5 drops in each affected ear

Inactive Ingredient

Glycerin

Other information

- recap bottle after each use
- keep away from head or direct sunlight
- store at room temperature 15-25ºC (59-77ºF)
- do not use if foil seal imprinted with “SEALED FOR YOUR PROTECTION” under cap is broken or missing
- keep carton for full drug facts

Questions?

1-800-344-7239 debrox.com

Principal Display Panel

Debrox ® Swimmer’s Ear
Isopropyl alcohol 95%
Ear Drying Drops
1 FL OZ (30 mL)